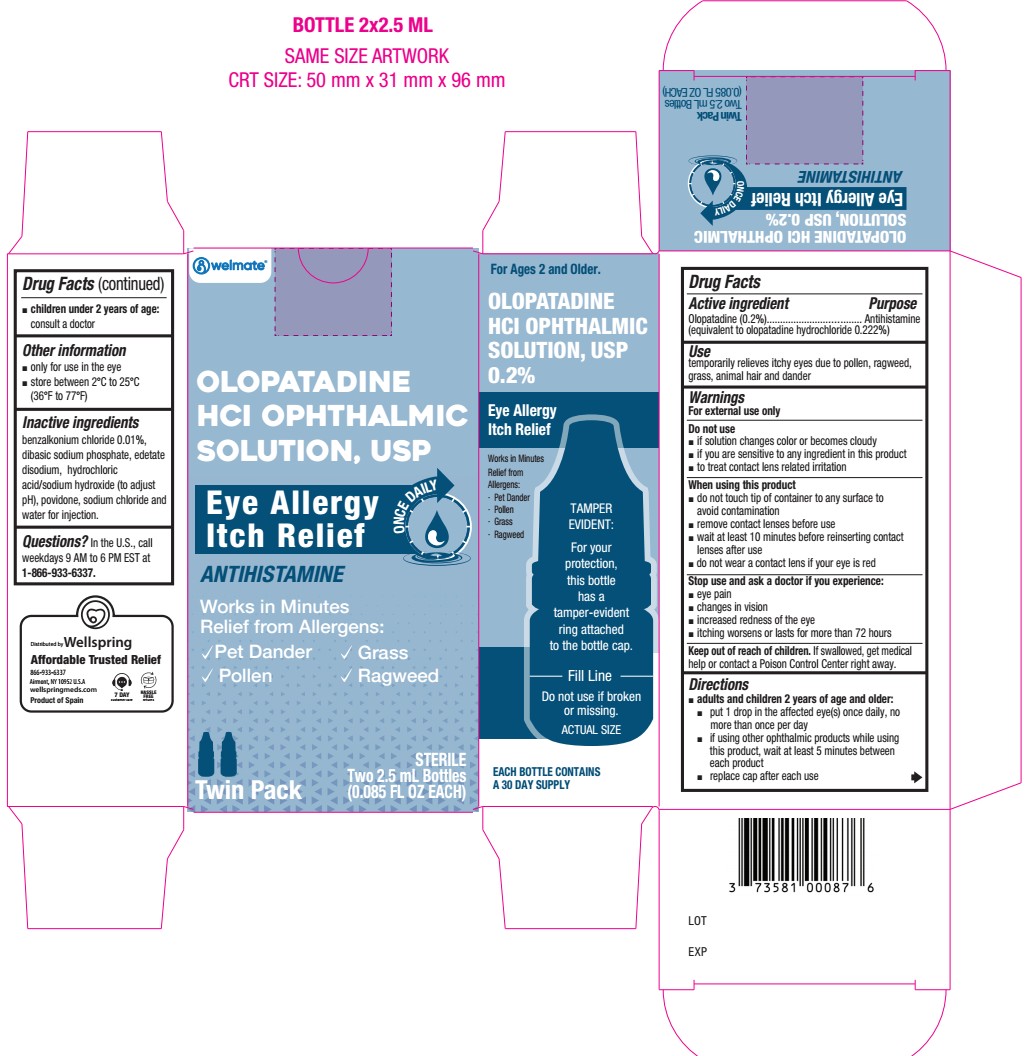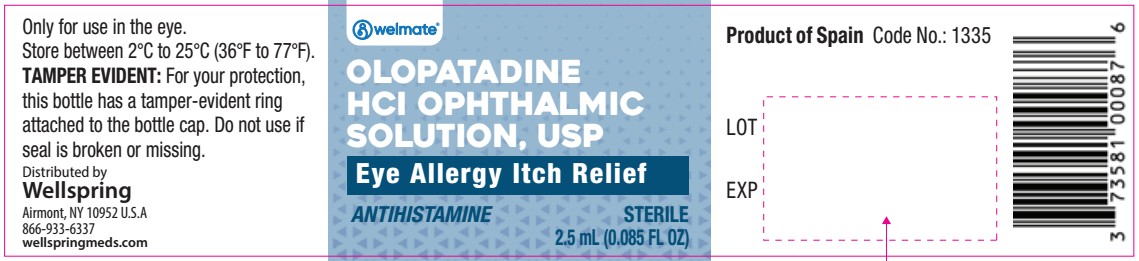 DRUG LABEL: OLOPATADINE HYDROCHLORIDE
NDC: 73581-709 | Form: SOLUTION
Manufacturer: YYBA Corp
Category: otc | Type: HUMAN OTC DRUG LABEL
Date: 20260203

ACTIVE INGREDIENTS: OLOPATADINE HYDROCHLORIDE 2 mg/1 mL
INACTIVE INGREDIENTS: EDETATE DISODIUM; POVIDONE K30; SODIUM HYDROXIDE; SODIUM CHLORIDE; BENZALKONIUM CHLORIDE; HYDROCHLORIC ACID; SODIUM PHOSPHATE, DIBASIC, ANHYDROUS; WATER

Olopatadine 2%

ACTIVE INGREDIENT

Active Ingredients - Purpose - Olopatadine 0.2% (equivalent to olopatadine hydrochloride 0.222%) Antihistamine

Active Ingredients | Purpose
Olopatadine 0.2% (equivalent to olopatadine hydrochloride 0.222%) | Antihistamine

Use

temporarily relieves itchy eyes due to pollen, ragweed, grass, animal hair and dander

Warnings

For external use only

Do not use

- if solution changes color or becomes cloudy
- if you are sensitive to any ingredient in this product
- to treat contact lens related irritation

When using this product

- do not touch tip of container to any surface to avoid contamination
- remove contact lenses before use
- wait at least 10 minutes before reinserting contact lenses after use
- do not wear a contact lens if your eye is red

Stop use and ask a doctor if

- eye pain
- changes in vision
- increased redness of the eye
- itching worsens or lasts for more than 72 hours

Keep out of reach of children. If swallowed, get medical help or contact a Poison Control Center right away.

Directions

- adults and children 2 years of age and older:
- put 1 drop in the affected eye(s) once daily, no more than once per day
- if using other ophthalmic products while using this product, wait at least 5 minutes between each product
- replace cap after each use

- children under 2 years of age: consult a doctor

Other information

- only for use in the eye
- store between 2°C to 25°C (36°F to 77°F)

Inactive ingredients

benzalkonium chloride 0.01%, dibasic sodium phosphate, edetate disodium, hydrochloric acid/sodium hydroxide (to adjust pH), povidone, sodium chloride and water for injection

Questions?

In the U.S., call toll free weekdays 9 AM to 6 PM EST at 1 (866) 933-6337.

Distributed by:

Wellspring Meds USA

Airmont, NY 10952

PACKAGE LABEL

Olopatadine hydrochloride
ophthalmic solution 0.2%

Antihistamine
2.5 mL
STERILE

EYE ALLERGY ITCH RELIEF

Original Prescription Strength
ONCE DAILY RELIEF
Olopatadine hydrochloride ophthalmic solution 0.2%
Antihistamine
Eye Allergy Itch Relief

STERILE
2.5 mL